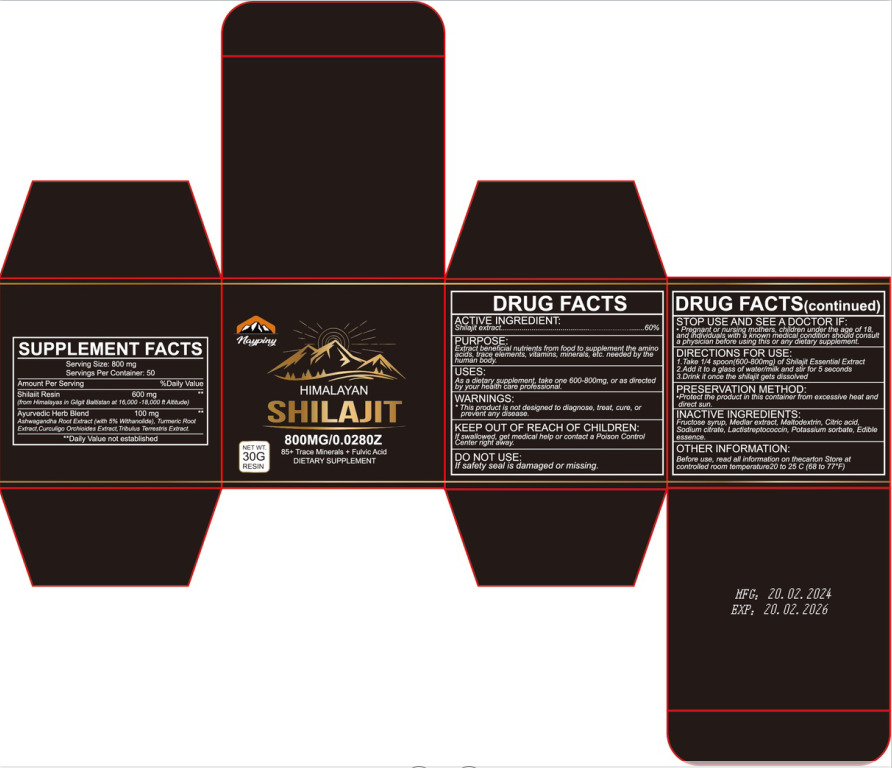 DRUG LABEL: Shilajit
NDC: 84322-005 | Form: CREAM
Manufacturer: Shenzhen Gaoye E-commerce Co., Ltd
Category: otc | Type: HUMAN OTC DRUG LABEL
Date: 20240730

ACTIVE INGREDIENTS: FULVIC ACID 60 g/100 g
INACTIVE INGREDIENTS: ANHYDROUS CITRIC ACID; ETHYL METHYLPHENYLGLYCIDATE; TRISODIUM CITRATE DIHYDRATE; NISIN; POTASSIUM SORBATE; MALTOSE ANHYDROUS; BETAINE; MALTODEXTRIN

84322-005

Active Ingredient(s)

Shilajit extract 60%

Purpose

Extract beneficial nutrients from food to supplement the amino acids, trace elements, vitamins, minerals, etc. needed by the human body.

Use

As a dietary supplement, take one 600-800mg, or as directed by your health care professional.

Warnings

This product is not designed to diagnose, treat, cure, or prevent any disease.

Do not use

If safety seal is damaged or missing.

WHEN USING

In case of contact with eyes, rinse eyes thoroughly with water.

STOP USE

Pregnant or nursing mothers, children under the age of 18, and individuals with a known medical condition should consult a physician before using this or any dietary supplement.

KEEP OUT OF REACH OF CHILDREN

If swallowed, get medical help or contact a Poison Control Center right away.

Directions

1. Take 1/4 spoon(600-800mg) of Shilajit Essential Extract

2. Add it to a glass of water/milk and stir for 5 seconds
3. Drink it once the shilajit gets dissolved

Other information

Before use, read all information on thecarton Store at controlled room temperature20 to 25 C (68 to 77°F)

Inactive ingredients

Fructose syrup, Medlar extract, Maltodextrin, Citric acid, Sodium citrate, Lactistreptococcin, Potassium sorbate, Edible essence.